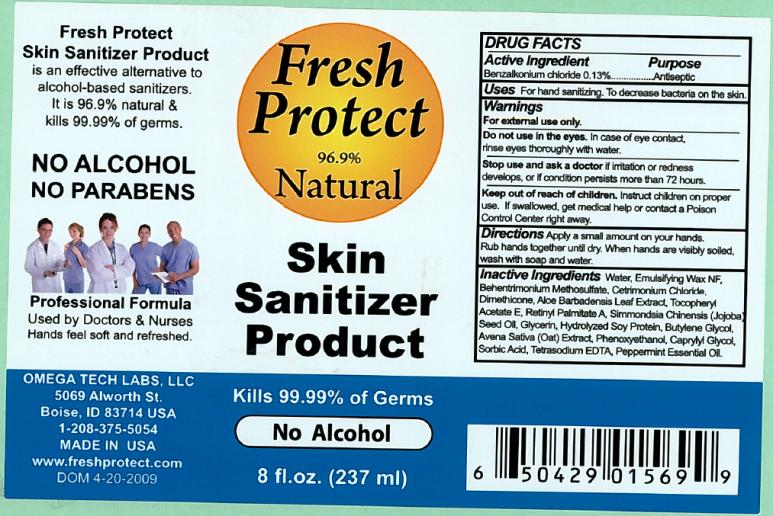 DRUG LABEL: Fresh Protect Skin Sanitizer
NDC: 20802-1500 | Form: LOTION
Manufacturer: Omega Tech Labs Inc.
Category: otc | Type: HUMAN OTC DRUG LABEL
Date: 20110102

ACTIVE INGREDIENTS: BENZALKONIUM CHLORIDE .0013 g/1 mL
INACTIVE INGREDIENTS: WATER; BEHENTRIMONIUM METHOSULFATE; CETRIMONIUM CHLORIDE; DIMETHICONE; ALOE VERA LEAF; ALPHA-TOCOPHEROL ACETATE; VITAMIN A PALMITATE; JOJOBA OIL; GLYCERIN; SOY PROTEIN; BUTYLENE GLYCOL; AVENA SATIVA LEAF; PHENOXYETHANOL; CAPRYLYL GLYCOL; SORBIC ACID; EDETATE SODIUM; PEPPERMINT OIL

Fresh Protect Skin Sanitizer Product

DRUG FACTS

Active Ingredient

Benzalkonium chloride 0.13%

Purpose

Antiseptic

Uses

For hand sanitizing. To decrease bacteria on the skin.

Warnings

For external use only.

Do not use

in the eyes. In case of eye contact, rinse eyes thoroughly with water.

Stop use and ask a doctor

if irritation or redness develops, or if condition persists more than 72 hours.

Keep out of reach of children.

Instruct children on proper use. If swallowed, get medical help or contact a Poison Control Center right away.

Directions

Apply a small amount on your hands. Rub hands together until dry. When hands are visibly soiled, wash with soap and water.

Inactive Ingredients

Water, Emulsifying Wax NF, Behentrimonium Methosulfate, Centrimonium Chloride, Dimethicone, Aloe Barbadensis Leaf Extract, Tocopheryl Acetate E, Retinyl Palmitate A, Simmondsia Chinensis (Jojoba) Seed Oil, Glycerin, Hydrolyzed Soy Protein, Butylene Glycol, Avena Sativa (Oat) Extract, Phenoxyethanol, Caprylyl Glycol, Sorbic Acid, Tetrasodium EDTA, Peppermint Essential Oil.

PRINCIPAL DISPLAY PANEL

Fresh Protect
96.9% Natural
Skin Sanitizer Product
Kills 99.99% of Germs
No Alcohol
8 fl. oz. (237 ml)